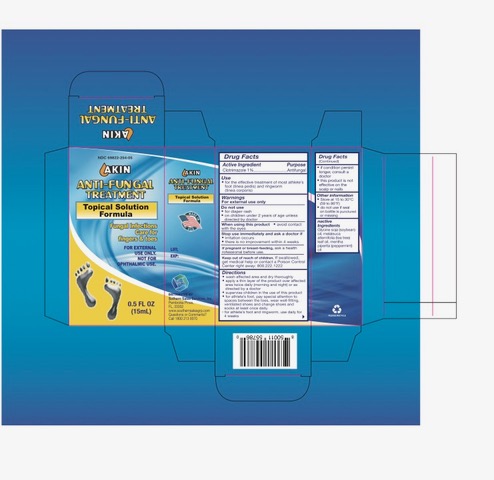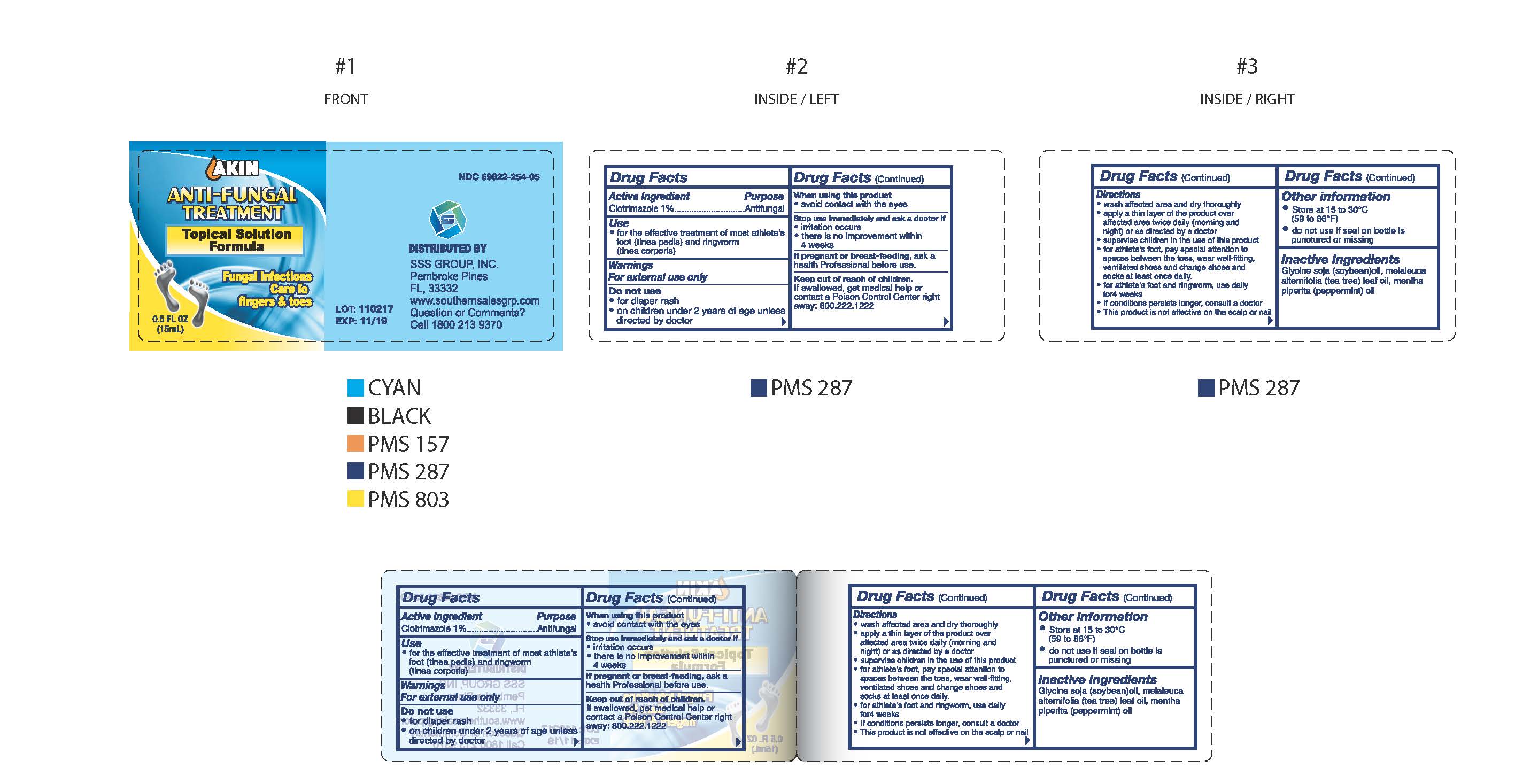 DRUG LABEL: AKIN ANTI-FUNGAL
NDC: 69822-254 | Form: SOLUTION
Manufacturer: Southern Sales & Service, Inc.
Category: otc | Type: HUMAN OTC DRUG LABEL
Date: 20231129

ACTIVE INGREDIENTS: CLOTRIMAZOLE 10 mg/1 mL
INACTIVE INGREDIENTS: SOYBEAN OIL; MELALEUCA ALTERNIFOLIA LEAF; MENTHA PIPERITA

AKIN Anti-Fungal Treatment

Drug Facts

Active Ingredient

Clotrimazole 1%

Purpose

Antifungal

Use

for the effective treatment of most athlete's foot (tinea pedis) and ringworm (tinea corporis)

Warnings

For external use only

Do not use

- for diaper rash
- on children under 2 years of age unless directed by doctor

When using this product

- avoid contact with the eyes

Stop use immediately and ask a doctor if

- irritation occurs
- there is no improvement within 4 weeks

If pregnant or breast-feeding,

ask a health rofessional before use.

Keep out of reach of children.

If swallowed, get medical help or contact a Poison Control Center right away. 800.222.1222

Directions

- wash affected area and dry thoroughly
- apply a thin layer of the product over affeceted area twice daily (morning and night) or as directed by a doctor
- supervise children in the use of this product
- for athlete's foot, pay special attention to spaces between the toes, wear well-fitting, ventilated shoes and change shoes and socks at least once daily.
- for athlete's foot and ringworm, use daily for 4 weeks
- if condition persists longer, consult a doctor
- this product is not effective on the scalp or nails

Other information

- Store at 15 to 30 °C (59 to 86 °F)
- do not use if seal on bottle is punctured or missing

Inactive Ingredients

Glycine soja (soybean) oil, melaleuca alternifolia (tea tree) leaf oil, metha piperita (perpperminta) oil